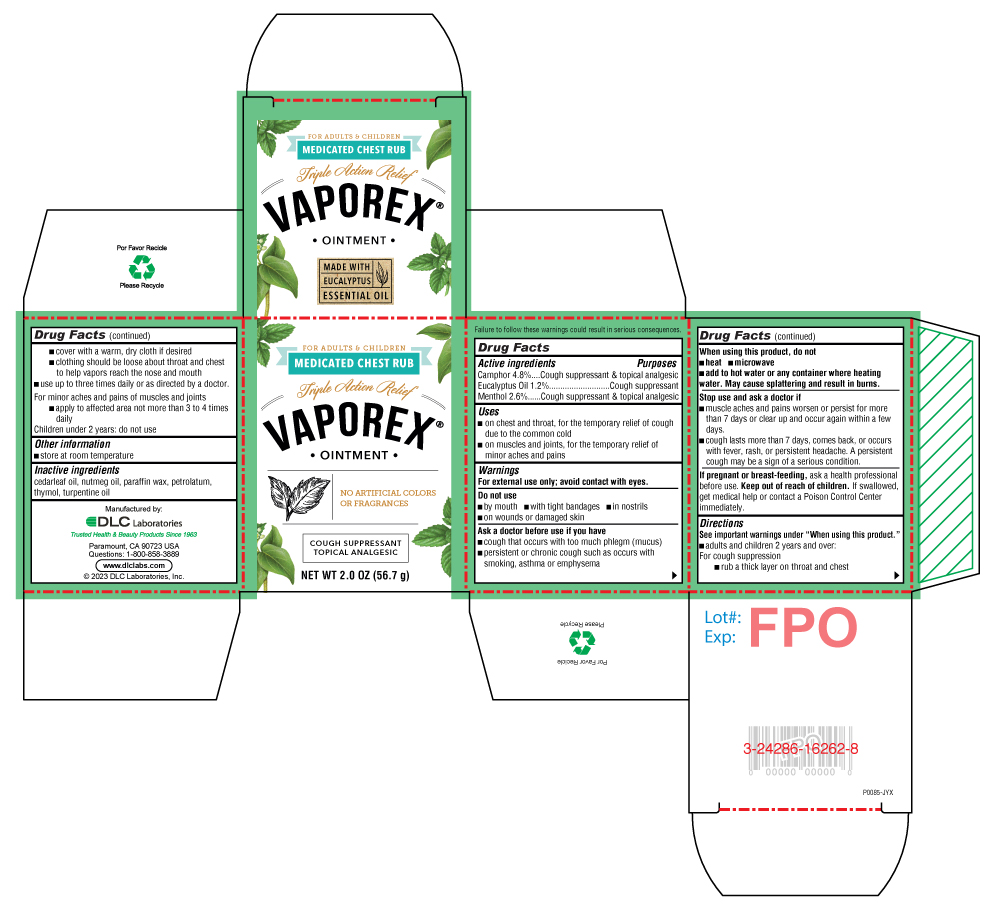 DRUG LABEL: VAPOREX
NDC: 24286-1564 | Form: OINTMENT
Manufacturer: DLC Laboratories, Inc.
Category: otc | Type: HUMAN OTC DRUG LABEL
Date: 20260107

ACTIVE INGREDIENTS: CAMPHOR (SYNTHETIC) 4.8 g/100 g; EUCALYPTUS OIL 1.2 g/100 g; MENTHOL, UNSPECIFIED FORM 2.6 g/100 g
INACTIVE INGREDIENTS: PARAFFIN; PETROLATUM; CEDAR LEAF OIL; NUTMEG OIL; THYMOL; TURPENTINE OIL

VAPOREX®

Drug Facts

ACTIVE INGREDIENT

PURPOSE

Active Ingredients | Purposes
Camphor 4.8% | Cough suppressant & topical analgesic
Eucalyptus Oil 1.2% | Cough suppressant
Menthol 2.6% | Cough suppressant & topical analgesic

Uses

- on chest and throat, for the temporary relief of cough due to the common cold
- on muscles and joints, for the temporary relief of minor aches and pains

Warnings

For external use only; avoid contact with eyes.

Do not use

- by mouth
- with tight bandages
- in nostrils
- on wounds or damaged skin

Ask a doctor before use if you have

- cough that occurs with too much phlegm (mucus)
- persistent or chronic cough such as occurs with smoking, asthma or emphysema

When using this product, do not

- heat
- microwave
- add to hot water or any container where heating water. May cause splattering and result in burns.

Stop use and ask a doctor if

- muscle aches and pains worsen or persist for more than 7 days or clear up and occur again within a few days.
- cough lasts more than 7 days, comes back, or occurs with fever, rash, or persistent headache. A persistent cough may be a sign of a serious condition.

PREGNANCY OR BREAST FEEDING

If pregnant or breast-feeding,ask a health professional before use.

Keep out of reach of children.If swallowed, get medical help or contact a Poison Control Center immediately.

Directions

See important warnings under "When using this product."

- adults and children 2 years and over:
  For cough suppression
  - rub a thick layer on throat and chest
  - cover with a warm, dry cloth if desired
  - clothing should be loose about throat and chest to help vapors reach the nose and mouth
- use up to three times daily or as directed by a doctor.
  For minor aches and pains of muscles and joints
  - apply to affected area not more than 3 to 4 times daily

Children under 2 years: do not use

Other information

- store at room temperature

Inactive ingredients

cedarleaf oil, nutmeg oil, paraffin wax, petrolatum, thymol, turpentine oil

Manufactured by:
DLC Laboratories
Paramount, CA 90723 USA

PRINCIPAL DISPLAY PANEL - 56.7 g Jar Carton

FOR ADULTS & CHILDREN

MEDICATED CHEST RUB

Triple Action Relief

VAPOREX®

• OINTMENT •

NO ARTIFICIAL COLORS
OR FRAGRANCES

COUGH SUPPRESSANT
TOPICAL ANALGESIC

NET WT 2.0 OZ (56.7 g)